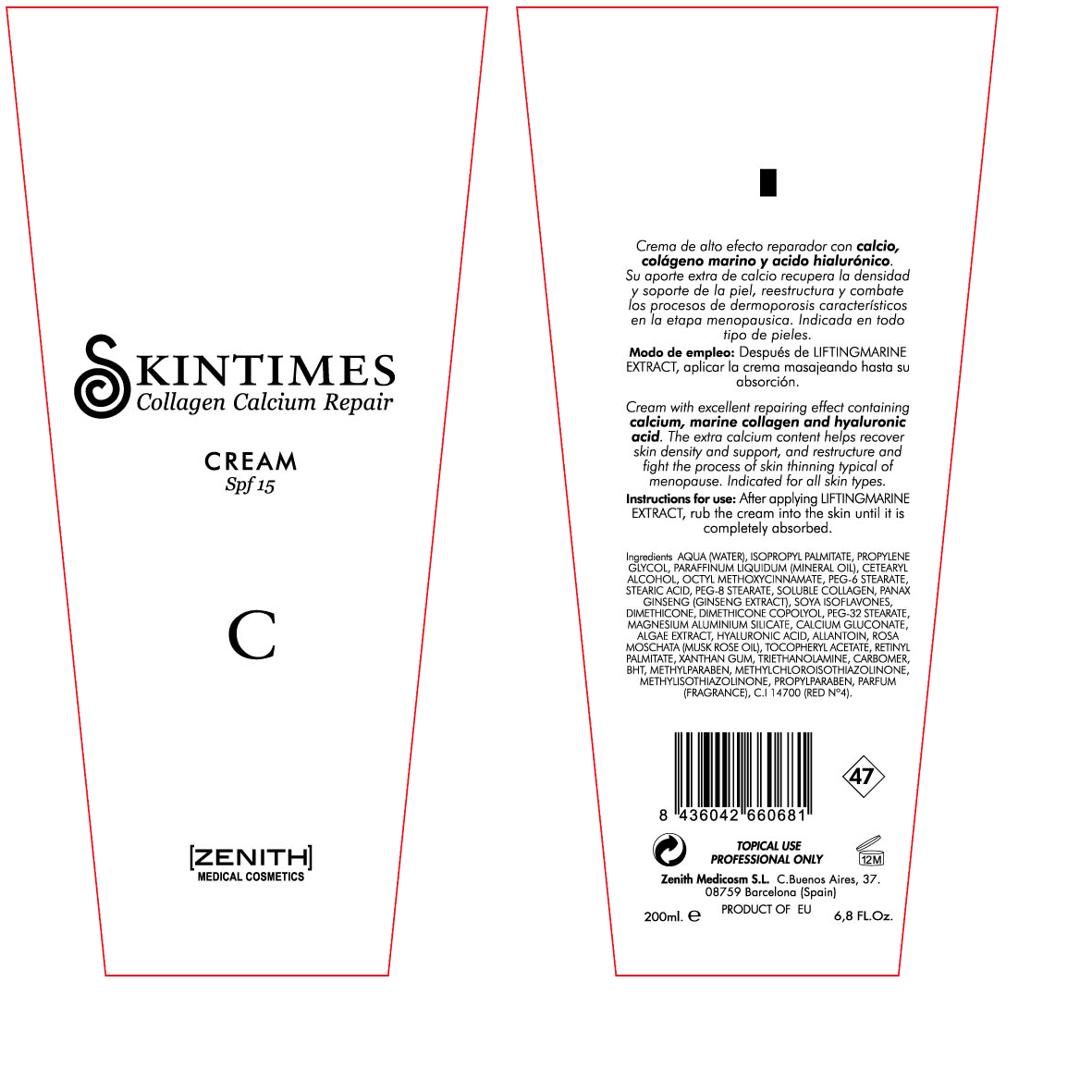 DRUG LABEL: Calcium
NDC: 42248-116 | Form: CREAM
Manufacturer: Zenith Medicosm SL
Category: otc | Type: HUMAN OTC DRUG LABEL
Date: 20120121

ACTIVE INGREDIENTS: OCTINOXATE 15 mL/200 mL
INACTIVE INGREDIENTS: MAGNESIUM ALUMINUM SILICATE; PROPYLPARABEN; ALPHA-TOCOPHEROL ACETATE; DIMETHICONE; XANTHAN GUM; ROSA MOSCHATA OIL; WATER; MINERAL OIL; CETOSTEARYL ALCOHOL; PEG-8 STEARATE; TROLAMINE; SOY ISOFLAVONES; CALCIUM GLUCONATE; BUTYLATED HYDROXYTOLUENE; HYALURONIC ACID; CARBOMER 934; METHYLPARABEN; COLLAGEN, SOLUBLE, FISH SKIN; ISOPROPYL PALMITATE; PEG-6 STEARATE; PEG-32 STEARATE; STEARIC ACID; PANAX GINSENG FRUIT; FUCUS VESICULOSUS; ALLANTOIN; VITAMIN A PALMITATE; PROPYLENE GLYCOL; METHYLCHLOROISOTHIAZOLINONE; METHYLISOTHIAZOLINONE; FD&C RED NO. 4

Drug Facts

Active Ingredient

Octinoxate 7.5%

Description

Cream with excellent repairing effect containing calcium, marine collagen and hyaluronic acid. The extra calcium content helps recover skin density and support, and restructure and fight the premature signs of skin thinning typical of menopause. Indicated for all skin types.

200ml. 6.8Fl.Oz

Warning

TOPICAL USE

PROFESSIONAL ONLY

Instructions for use:

After applying LIFTINGMARINE EXTRACT, rub the cream into the skin until it is completely absorbed.